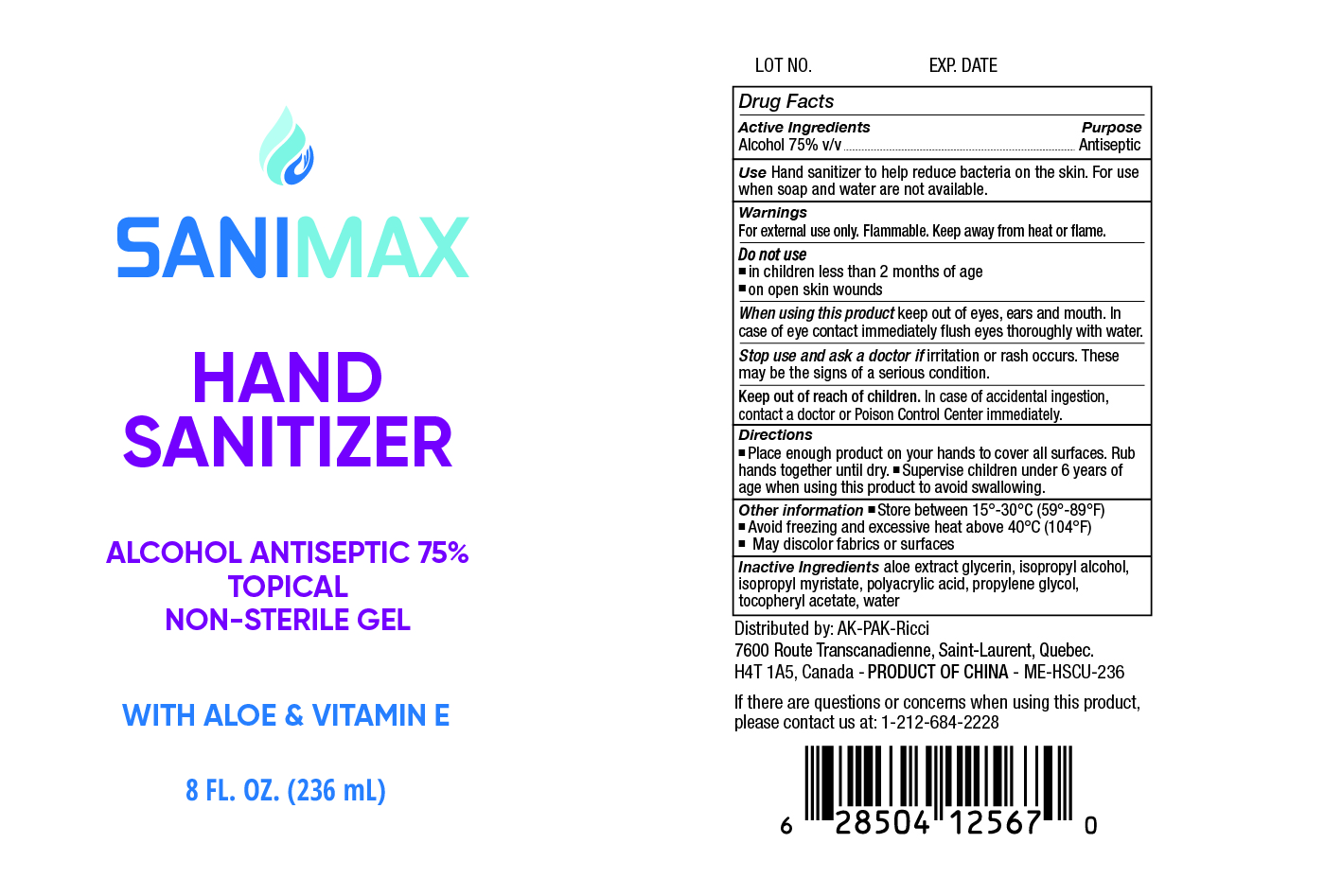 DRUG LABEL: Sanimax Hand Sanitizer
NDC: 74585-001 | Form: LIQUID
Manufacturer: AK-PAK-Ricci
Category: otc | Type: HUMAN OTC DRUG LABEL
Date: 20200629

ACTIVE INGREDIENTS: ALCOHOL 75 mL/100 mL
INACTIVE INGREDIENTS: ALOE; GLYCERIN; WATER; ISOPROPYL MYRISTATE; ISOPROPYL ALCOHOL; .ALPHA.-TOCOPHEROL ACETATE; PROPYLENE GLYCOL; POLYACRYLIC ACID (250000 MW)

Sanimax Hand Sanitizer

Active Ingredient

Alcohol 75% v/v

Purpose

Antiseptic

Use

Hand sanitizer to help reduce bacteria on the skin. For use when soap and water are not available

Warnings

For external use only. Flammable. Keep away from fire and flame.

Do not use

■ on children less than 2 months of age ■ on open skin wounds

When using this product

keep out of eyes, ears, and mouth. In case of eye contact, immediately flush eyes thoriughly with water.

Stop use and ask a doctor if

irritation or rash occurs. These may be signs of a serious condition

Keep out of reach of children

In case of accidential ingestion, contact a doctor or Poison Control Center immediately.

Directions

■ Place enough product on your hands to cover all surfaces. Rub hands together until dry ■ Supervise children under 6 years of age when using this product to avoid swallowing

Other information

■ Store between 15º- 30º (59-86ºF). ■ Avoid freezing and excessive heat above 40º (104ºF) ■ May discolor fabrics or surfaces

Inactive Ingredients

aloe extract, glycerin, isopropyl alcohol, isopropyl myristate, polyacrylic acid, propylene glycol, tocopheryl acetate, water.